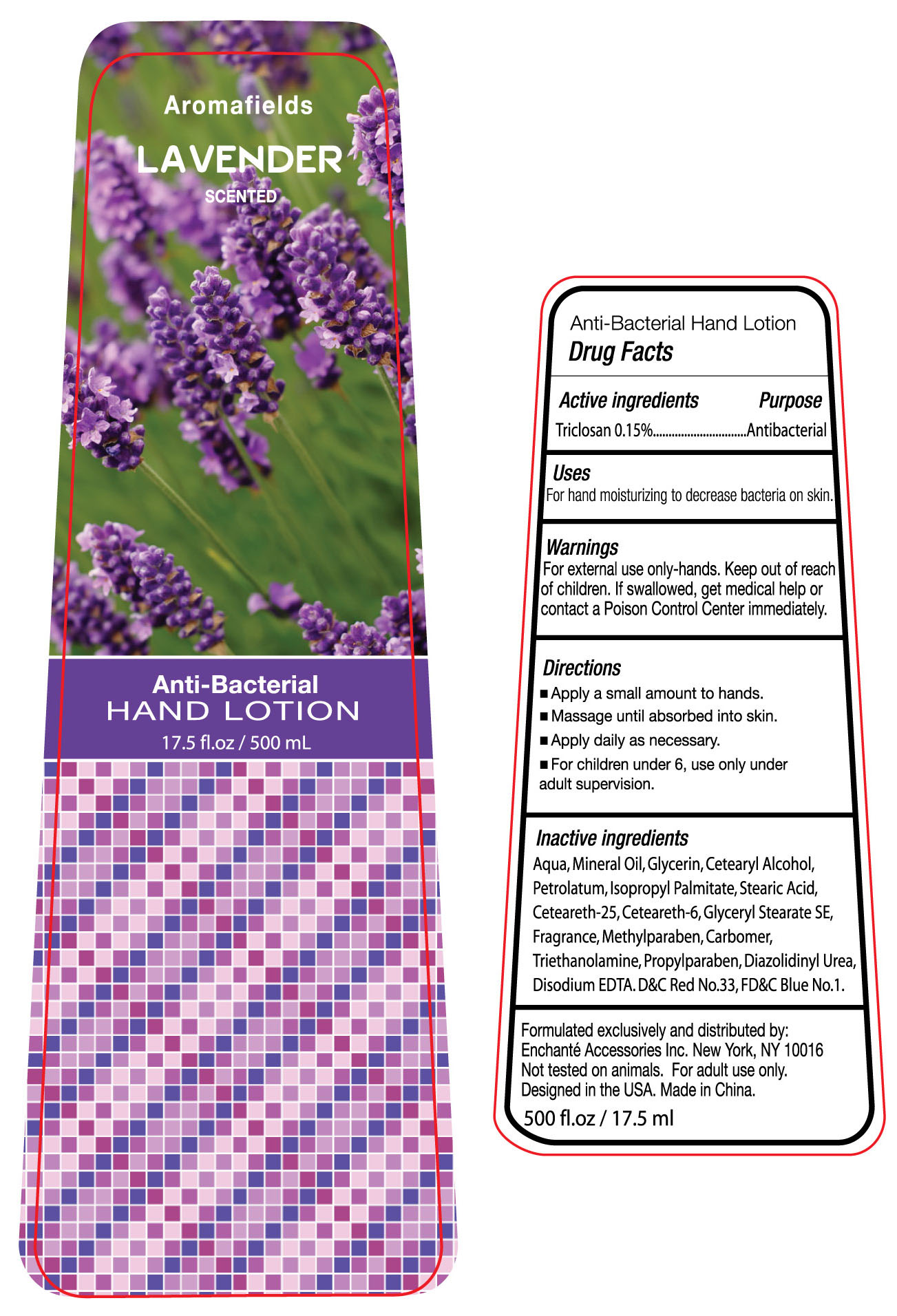 DRUG LABEL: Aromafields Lavender Scented Anti-Bacterial Hand 
NDC: 49371-045 | Form: LOTION
Manufacturer: ALILY (ZHANGZHOU) BATH PRODUCTS LTD.
Category: otc | Type: HUMAN OTC DRUG LABEL
Date: 20100608

ACTIVE INGREDIENTS: TRICLOSAN 0.15 g/100 g
INACTIVE INGREDIENTS: WATER 82.1095 g/100 g; GLYCERIN 3 g/100 g; TROLAMINE 0.12 g/100 g; MINERAL OIL 5 g/100 g; CETOSTEARYL ALCOHOL 2.5 g/100 g; PETROLATUM 1.5 g/100 g; D&C RED NO. 33 0.0004 g/100 g; FD&C BLUE NO. 1 0.0001 g/100 g; ISOPROPYL PALMITATE 1.0 g/100 g; STEARIC ACID 1.0 g/100 g; CETEARETH-30 1.0 g/100 g; CETEARETH-12 1.0 g/100 g; GLYCERYL MONOSTEARATE 0.8 g/100 g; METHYLPARABEN 0.2 g/100 g; CARBOMER HOMOPOLYMER TYPE A 0.12 g/100 g; PROPYLPARABEN 0.1 g/100 g; DIAZOLIDINYL UREA 0.1 g/100 g; EDETATE DISODIUM 0.1 g/100 g; LAVENDER 0.2 g/100 g

Drug Fact

Active Ingredient Purpose

Triclosan 0.15% Antiseptic

Uses:

- For hand moisturizing to decrease bacteria on the skin

Warnings:

For external use only. Keep out of reach of children. If swallowed, get medical help or contact a Poison Control Center immediately

Directions

- Apply a small amount to hands
- Massage until absorbed into skin
- Apply daily as necessary
- For children under 6, use only under adult supervision

Inactive Ingredients

Water (aqua), Mineral Oil, Glycerin, Cetearyl Alcohol, Petrolatum, Isopropyl Palmitate, Stearic Acid, Ceteareth-25, Cetearith-6, Glyceryl Stearate SE, Fragrance, Methylparaben, Carbomer, Triethanolamine, Propylparaben, Diazolidinyl Urea, Disodium EDTA, D and C Red No. 33, FD and C Blue No. 1

PACKAGE LABEL

pi